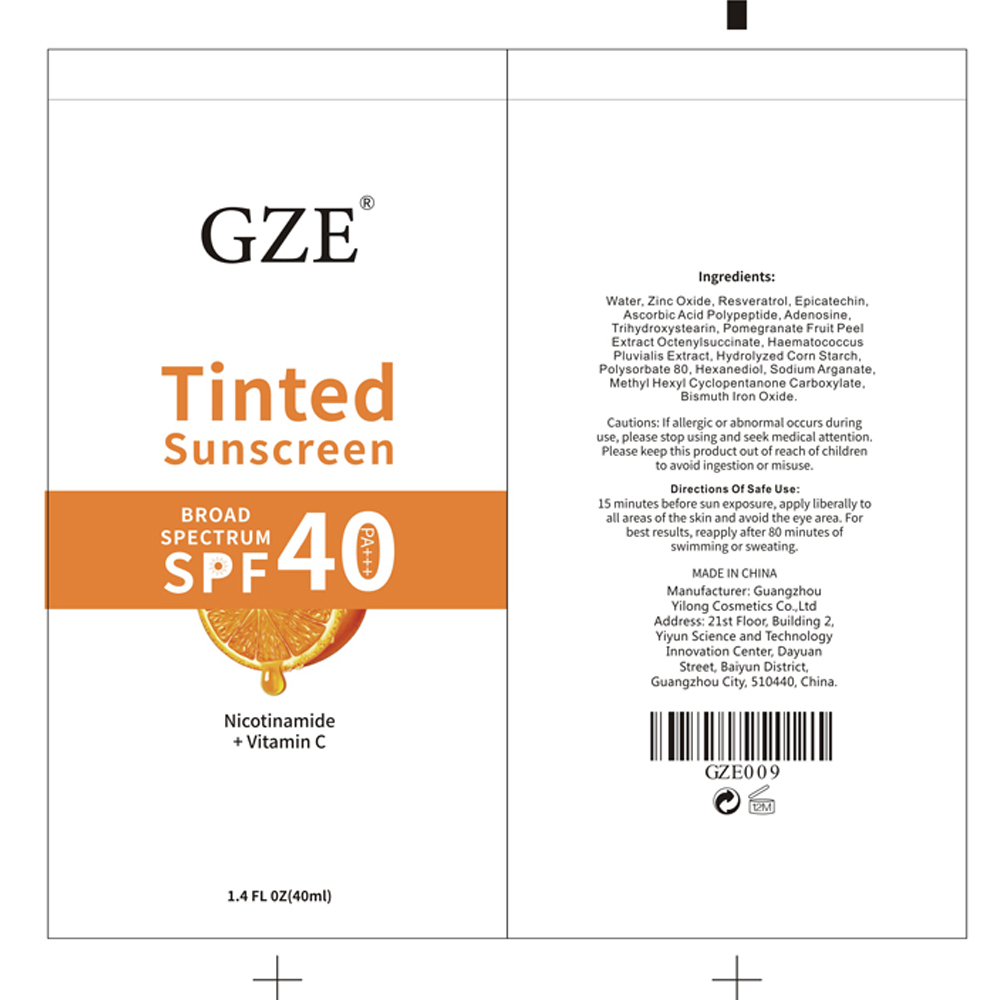 DRUG LABEL: GZE Tinted Sunscreen
NDC: 83566-100 | Form: CREAM
Manufacturer: Guangzhou Yilong Cosmetics Co.,Ltd.
Category: otc | Type: HUMAN OTC DRUG LABEL
Date: 20250715

ACTIVE INGREDIENTS: ZINC OXIDE 3 mg/100 mL
INACTIVE INGREDIENTS: LAUROYL LYSINE; ASCORBYL TETRAISOPALMITATE; ALPHA-TOCOPHEROL ACETATE; TRIETHOXYCAPRYLYLSILANE; PEG-12 DIMETHICONE; EPICATECHIN; HEXANEDIOL; POLYSORBATE 80; LEVOMENOL; TRIHYDROXYSTEARIN; SALIX ALBA BARK; RESVERATROL; CAPRYLIC ALCOHOL; FERRIC OXIDE RED; PHENOXYETHANOL; EDETATE DISODIUM; POMEGRANATE; MALTOTETRAOSE; WATER; HAEMATOCOCCUS PLUVIALIS; ISOPROPYL TITANIUM TRIISOSTEARATE; SOY ISOFLAVONES; ADENOSINE; ETHYLHEXYLGLYCERIN; ALKYL (C12-15) BENZOATE; DIMETHICONE

GZE Tinted Sunscreen

GZE Tinted Sunscreen

ACTIVE INGREDIENT

Zinc Oxide 3%

PURPOSE

HELPS PREVENT UV DAMAGE 8 SIGNS OF AGING

INDICATIONS AND USAGE

SILKY LOTION MATTIFIES WITH A SHEER, NATURAL TINT FOR ALL SKIN TONES

IHELPS PREVENTUV DAMAGE& SIGNS OF AGING

WARNINGS

For exteral use only, if it gets into eves accidentally, rinse with plenty of water, seek medical attention immediately if you feel unwell.Keep out of reach of children.

WHEN USING

Super-Light Daily Wrinkle Defense

INSTANTLY OBTAlN seemingly flawless, glowingskin. Perfect for that no-make up lOOK.FORMULATED AS AN ALLIN ONESUNSCREEN ANDFOUNDATiON that provides sheer color coverage minimizes the appearance of fine lines andwrinkles, and blendsnaturaly to match every sKintone.LIGHTWEIGHT AND NON-GREASY FORMULA thatimproves your skin's hydration and texture overtime.

STOP USE

For external use only, ifit gets into eyes accidentally, rinse with plenty of water, seek medical attention immediately if you feel unwell.Keep out of reach of children

Keep out of reach of children

DOSAGE AND ADMINISTRATION

Squeeze out an appropriate amount of sunscreen and spread evenly on skin

STORAGE AND HANDLING

Store in a cool dry place

INACTIVE INGREDIENT

Water

Polydimethylsiloxane

Peg Ppg-1818polydimethylsiloxane

DIMETHICONE

PEG-12 DIMETHICONE

Resveratrol

SOY ISOFLAVONES

Epicatechin

Tocopherol Acetate

ASCORBYL TETRAISOPALMITATE

Adenosine

LAUROYL LYSINE

Red Myrrh Alcohol

TRIHYDROXYSTEARIN

Barkextract Of Salixalba

Pomegranate Extract

Haematococcus Pluvialis Extract

Hydrolyzedcorn Starch

Polysorbate-80

Silica Triethoxy Octylsilane

C12-15 Alcohol Benzoate

Triisostearic Acidisopropyl Titanium Salt

Octanol

Hexanediol

Sodium Argon

Ethyl Hexyl Glycerol

2-Phenoxyethanol

lron Oxide